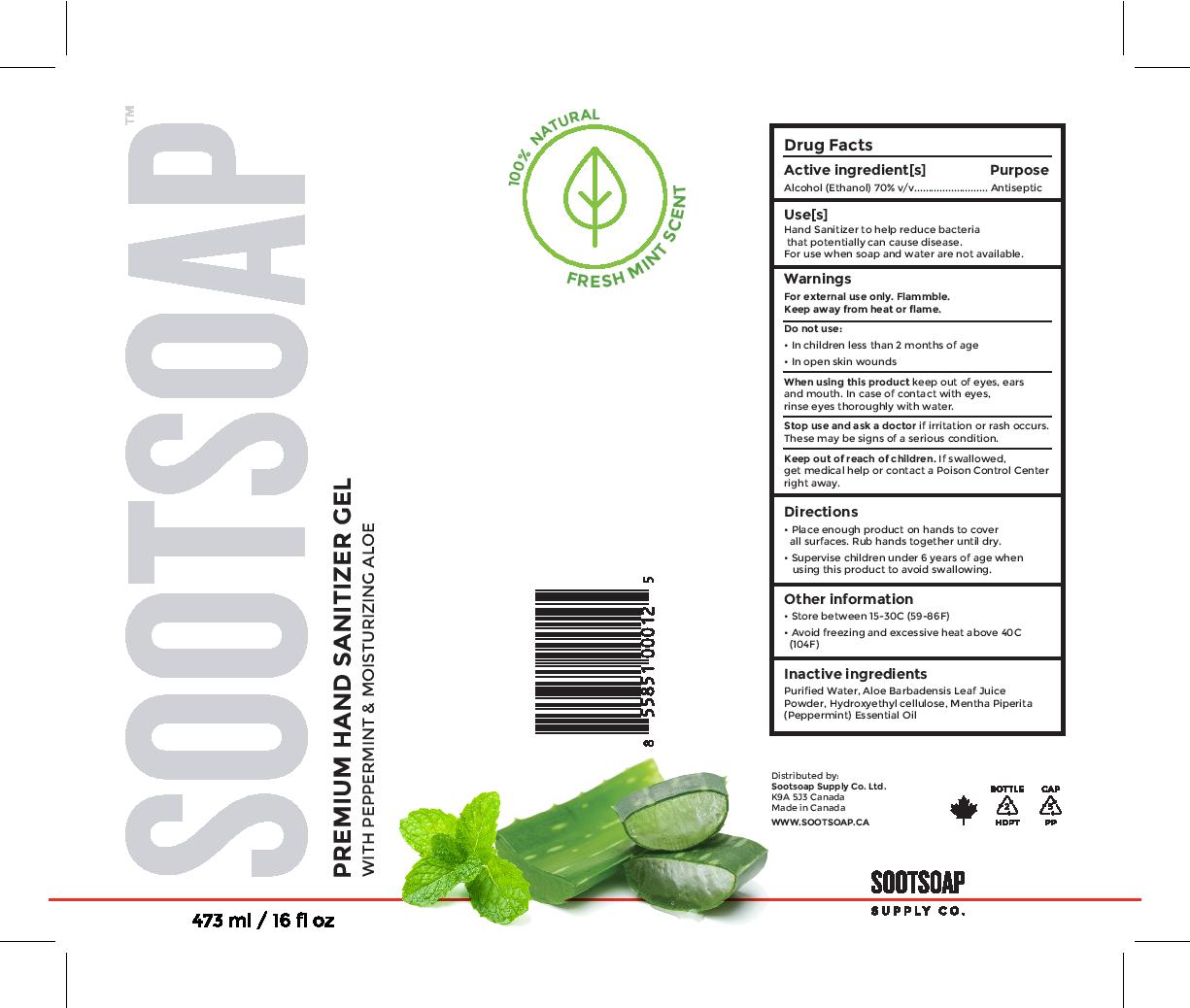 DRUG LABEL: Premium Hand Sanitizer Gel
NDC: 81524-111 | Form: GEL
Manufacturer: SOOTSOAP SUPPLY CO LTD
Category: otc | Type: HUMAN OTC DRUG LABEL
Date: 20240126

ACTIVE INGREDIENTS: ALCOHOL 70 mL/100 mL
INACTIVE INGREDIENTS: ALOE VERA LEAF; HYDROXYETHYL CELLULOSE, UNSPECIFIED; WATER; PEPPERMINT OIL

Directions

- Place enough product on hands to cover all surfaces. Rub hands together until dry.

- Supervise children under 6 years of age when using this product to avoid swallowing.

Inactive Ingredients

Purified water, Aloe Barbadensis Leaf Juice Powder, Hydroxyethyl cellulose, Mentha Piperita (Peppermint) Essential Oil

Uses

Hand Sanitizer to help reduce bacteria that potentially can cause disease.

For use when soap and water are not available.

Keep out of reach of children.

If swallowed, get medical help or contact a Poison Control Center right away.

Purpose

Antiseptic

Active Ingredient[s]

Alcohol (Ethanol) 70% v/v

Warnings

- For external use only. Flammable. Keep away from heat or flame.

- Do not use in children less than 2 months of age. Do not use in open skin wounds.

- When using this product keep out of eyes, ears and mouth. In case of contact with eyes, rinse eyes thoroughly with water.

- Stop use and ask a doctor if irritation or rash occurs. These may be signs of a serious condition.